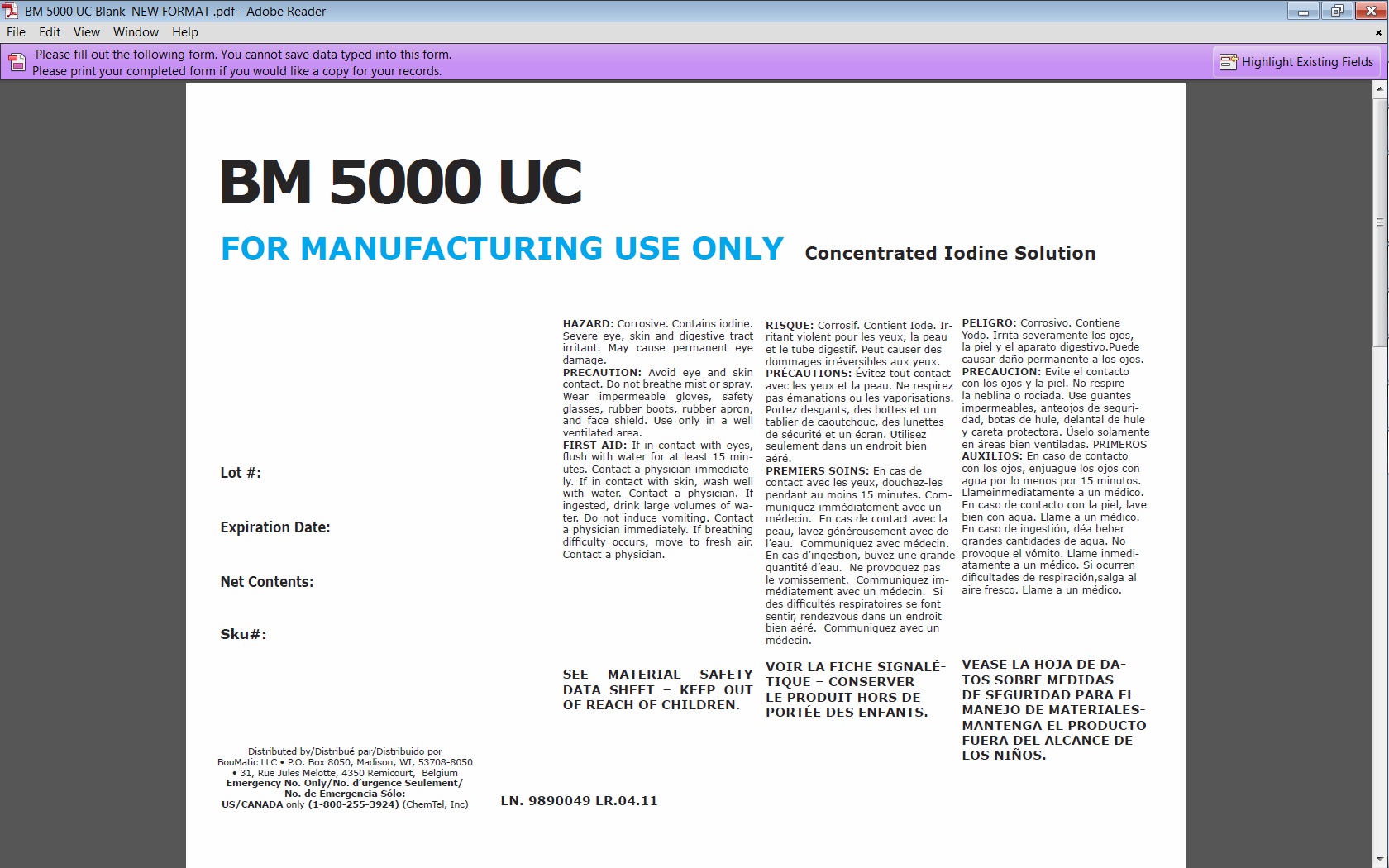 DRUG LABEL: BM 5000 UC
NDC: 48106-1171 | Form: LIQUID
Manufacturer: BouMatic, LLC
Category: animal | Type: OTC ANIMAL DRUG LABEL
Date: 20120101

ACTIVE INGREDIENTS: IODINE 550 mL/10 L

BM 5000 UC

PRECAUTIONS

HAZARD: Corrosive. Contains iodine. Severe eye, skin and digestive tract irritant. May cause permanent eye damage.
PRECAUTION: Avoid eye and skin contact. Do not breathe mist or spray. Wear impermeable gloves, safety glasses, rubber boots, rubber apron, and face shield. Use only in a well ventilated area.
FIRST AID: If in contact with eyes, flush with water for at least 15 minutes. Contact a physician immediately. If in contact with skin, wash well with water. Contact a physician. If ingested, drink large volumes of water. Do not induce vomiting. Contact a physician immediately. If breathing difficulty occurs, move to fresh air. Contact a physician.

SEE MATERIAL SAFETY DATA SHEET

BM 5000 UC label

INDICATIONS AND USAGE

FOR MANUFACTURING USE ONLY

Concentrated Iodine Solution